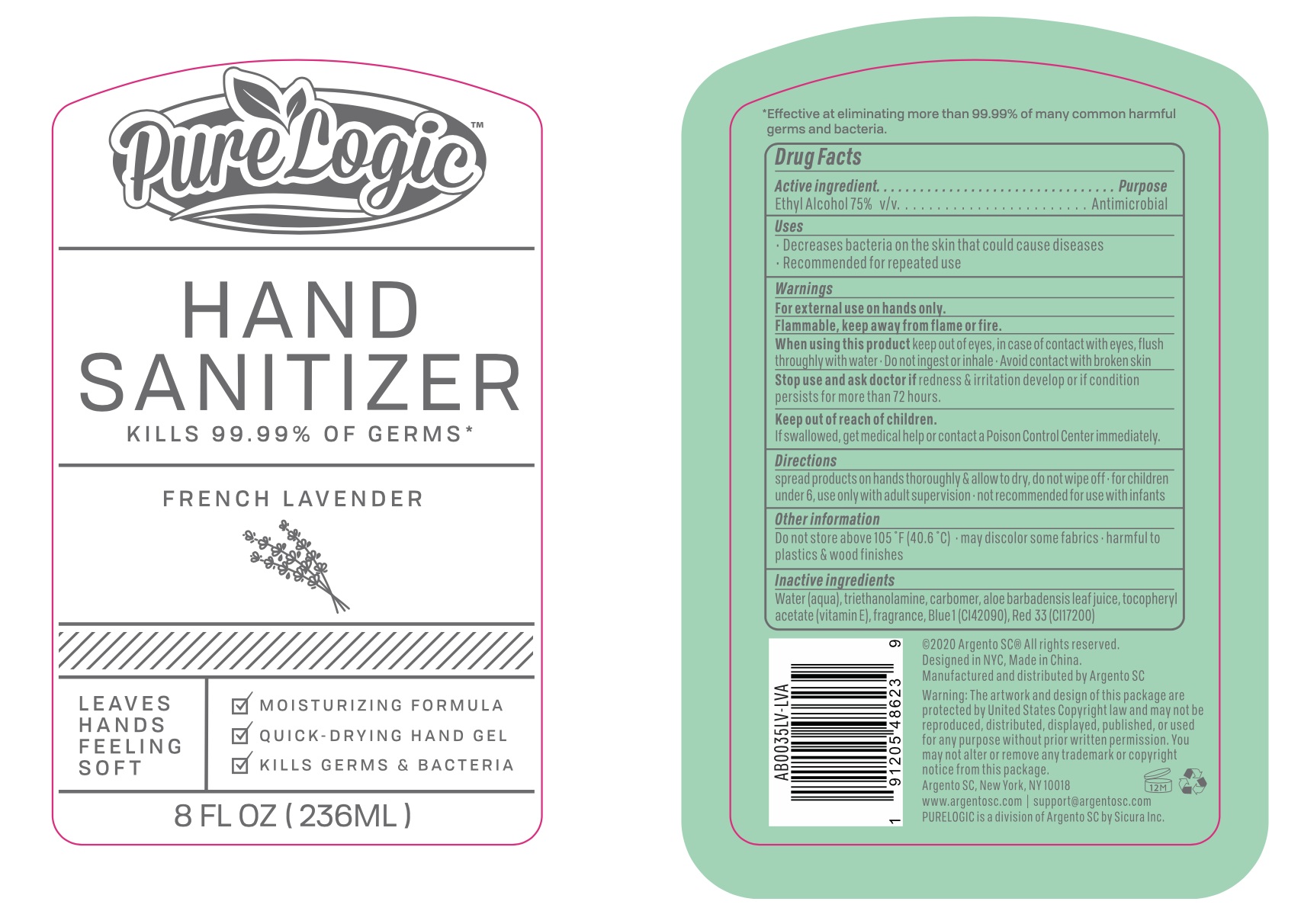 DRUG LABEL: PureLogic Hand Sanitizer French Lavender
NDC: 77731-082 | Form: SOLUTION
Manufacturer: Argento sc by sicura inc.
Category: otc | Type: HUMAN OTC DRUG LABEL
Date: 20200917

ACTIVE INGREDIENTS: ALCOHOL 75 mL/100 mL
INACTIVE INGREDIENTS: CARBOMER 940; TROLAMINE; WATER; ALOE VERA LEAF; .ALPHA.-TOCOPHEROL ACETATE; FD&C BLUE NO. 1; D&C RED NO. 33

77731-082/AB0035LV

Active Ingredient(s)

Ethyl Alcohol 75% v/v

Purpose:

Antimicrobial

Use

Decrease bacteria on skin that could cause diseases

Recommended for repeated use

Warnings

For external use only. Flammable, keep way from flame or fire

When using this product, keep out of eyes. In case of contact with eyes, flush thoroughly with water

Do not ingest or inhale

Avoid contact with broken skin

Stop use and ask a doctor

if irrigation and redness develop or if condition persists for more than 72 hours

Keep out of reach of children

if swallowed, get medical help or contact a Poison Control Center immediately

Directions

- Spread product on hands thoroughly and allow to dry, do not wipe off
- For children under 6, use under adult supervision
- Not recommended for use with infants

Other information

Do not store above 105F (40.6C)

May discolor some fabrics

Harmful to plastics and wood finishes

Inactive ingredients

Purified water, Carbomer, Triethanolamine, Aloe Barbadensis Leaf Juice, Tocopheryl Acetate (Vitamin E), Fragrance, Blue 1 (42090), Red 33 (CI17200)